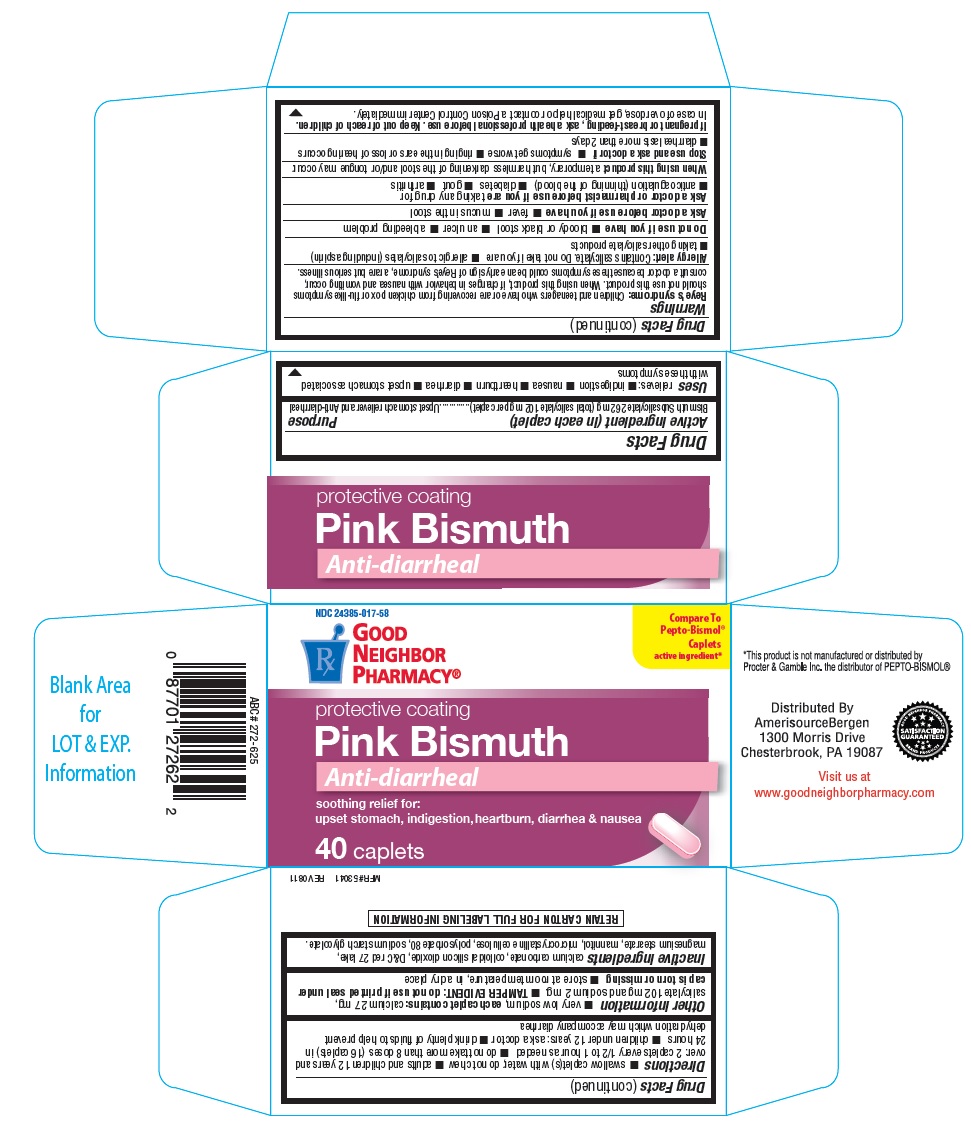 DRUG LABEL: GNP Pink Bismuth
NDC: 24385-017 | Form: TABLET
Manufacturer: Amerisource Bergen
Category: otc | Type: HUMAN OTC DRUG LABEL
Date: 20250120

ACTIVE INGREDIENTS: BISMUTH SUBSALICYLATE 262 mg/1 1
INACTIVE INGREDIENTS: CALCIUM CARBONATE; SILICON DIOXIDE; D&C RED NO. 27; MAGNESIUM STEARATE; MANNITOL; CELLULOSE, MICROCRYSTALLINE; POLYSORBATE 80; SODIUM STARCH GLYCOLATE TYPE A CORN

GNP Pink Bismuth tablets

Active ingredient (in each caplet)

Bismuth subsalicylate 262 mg

(total salicylate 102 mg per caplet)

Purpose

Upset stomach reliever and anti-diarrheal

Uses

relieves:

- indigestion
- nausea
- heartburn
- diarrhea
- upset stomach associated with these symptoms

Warnings

Reye's syndrome: Children and teenagers who have or are recovering from chicken pox or flu-like symptoms should not use this product. when using this product , if changes in behavior with nausea and vomiting occur, consult a doctor because these symptoms could be an early sign of Reye's syndrome, a rare but serious illness.

Allergy alert:Contains salicylate. Do not take if you are

allergic to salicylates (including aspirin)

taking other salicylate products

Do not use if you have

- bloody or black stool
- an ulcer
- a bleeding problem

Ask a doctor before use if you have

- fever
- mucus in the stool

Ask a doctor or pharmacist before use if you are taking any drug for

- anticoagulation (thinning of the blood)
- diabetes
- gout
- arthritis

When using this product

a temporary, but harmless darkening of the stool and/or tongue may occur.

Stop use and ask a doctor if

- symptoms get worse
- ringing in the ears or loss of hearing occurs
- diarrhea lasts more than 2 days

If pregnant or breast-feeding, ask a health professional before use. Keep out of reach of children.

In case of overdose, get medical help or contact a poison control center immediately.

Directions

- Swallow caplet(s) with water, do not chew
- adults and children 12 years and over: 2 caplets every 1/2 to 1 hour as needed
- do not take more than 8 doses (16 caplets) in 24 hours
- children under 12 years: ask a doctor
- drink plenty of fluids to help prevent dehydration which may accompany diarrhea.

Other information

- very low sodium, each caplet contains: calcium 27 mg, salicylate 102 mg and sodium 2 mg.
- TAMPER EVIDENT: Do not use if printed seal under cap is torn or missing.
- store at room temperature, in a dry place

Inactive ingredients

calcium carbonate, colloidal silicon dioxide, D&C red 27 aluminum lake, magnesium stearate, mannitol, microcrystalline cellulose, polysorbate 80, sodium starch glycolate.

PDP

Good Neighbor Pharmacy

COMPARE TO PEPTO-BISMOL® ACTIVE INGREDIENT

protective coating

Pink Bismuth

Soothing relief for

: upset stomach, indigestion, nausea, heartburn and diarrhea

40 caplets